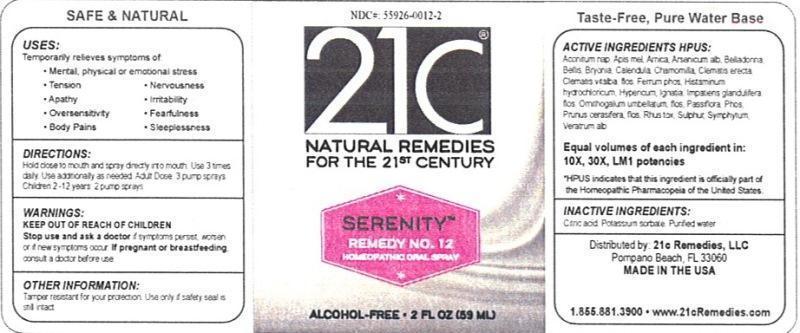 DRUG LABEL: Serenity Remedy No. 12
NDC: 55926-0012 | Form: LIQUID
Manufacturer: Speer Laboratories, LLC
Category: homeopathic | Type: HUMAN OTC DRUG LABEL
Date: 20130806

ACTIVE INGREDIENTS: ACONITUM NAPELLUS 10 [hp_X]/59 mL; APIS MELLIFERA 10 [hp_X]/59 mL; ARNICA MONTANA 10 [hp_X]/59 mL; ARSENIC TRIOXIDE 10 [hp_X]/59 mL; ATROPA BELLADONNA 10 [hp_X]/59 mL; BELLIS PERENNIS 10 [hp_X]/59 mL; BRYONIA ALBA ROOT 10 [hp_X]/59 mL; CALENDULA OFFICINALIS FLOWERING TOP 10 [hp_X]/59 mL; MATRICARIA RECUTITA 10 [hp_X]/59 mL; CLEMATIS RECTA FLOWERING TOP 10 [hp_X]/59 mL; CLEMATIS VITALBA FLOWER 10 [hp_X]/59 mL; FERROSOFERRIC PHOSPHATE 10 [hp_X]/59 mL; HISTAMINE DIHYDROCHLORIDE 10 [hp_X]/59 mL; HYPERICUM PERFORATUM 10 [hp_X]/59 mL; STRYCHNOS IGNATII SEED 10 [hp_X]/59 mL; IMPATIENS GLANDULIFERA FLOWER 10 [hp_X]/59 mL; ORNITHOGALUM UMBELLATUM FLOWERING TOP 10 [hp_X]/59 mL; PASSIFLORA INCARNATA FLOWERING TOP 10 [hp_X]/59 mL; PHOSPHORUS 10 [hp_X]/59 mL; PRUNUS CERASIFERA FLOWER 10 [hp_X]/59 mL; TOXICODENDRON PUBESCENS LEAF 10 [hp_X]/59 mL; SULFUR 10 [hp_X]/59 mL; COMFREY ROOT 10 [hp_X]/59 mL; VERATRUM ALBUM ROOT 10 [hp_X]/59 mL
INACTIVE INGREDIENTS: WATER; CITRIC ACID MONOHYDRATE; POTASSIUM SORBATE

Serenity Remedy No. 12

Active Ingredient HPUS: Aconitum napellus, Apis mellifica, Arnica montana, Arsenicum album, Belladonna, Bellis perennis, Bryonia, Calendula officinalis, Chamomilla, Clematis erecta, Clematis vitalba, flos, Ferrum phosphoricum, Histaminum hydrochloricum, Hypericum perforatum, Ignatia amara, Impatiens glandulifera, flos, ornithogalum umbellatum, flos, Passiflora incarnata, Phosphorus, Prunus cerasifera, flos, Rhus toxicodendron, sulphur, symphytum officinale, Veratrum album.

Equal volumes of each ingredient in: 10X, 30X, LM1 potencies.

HPUS indicates that this ingredient is officially part of the Homeopathic Pharmacopia of the United States.

Inactive Ingredients: Citric acid, Potassium sorbate, Purified water.

INDICATIONS AND USAGE

Uses: Temporarily relieves symptoms of:

- mental, physical or emotional stress
- tension
- apathy
- oversensitivity
- body pains
- nervousness
- irritability
- fearfulness
- sleepessness

DOSAGE AND ADMINISTRATION

Directions: Hold close to mouth and spray directly into mouth. Use 3 times daily. Use additionally as needed. Adult Dose: 3 pump sprays. Children 2-12 years: 2 pump sprays.

Keep out of reach of children.

Warnings:

Stop use and ask a doctor if symptoms persist, worsen or if new symptoms occur. If pregnant or breastfeeding, consult a doctor before use.

Other Information: Tamper resistant for your protection. Use only if safety seal is still intact.

PURPOSE

Uses: Temporarily relieves symptoms of: mental, physical or emotional stress, tension, apathy, oversensitivity, body pains, nervousness, irritability, fearfulness, sleepessness